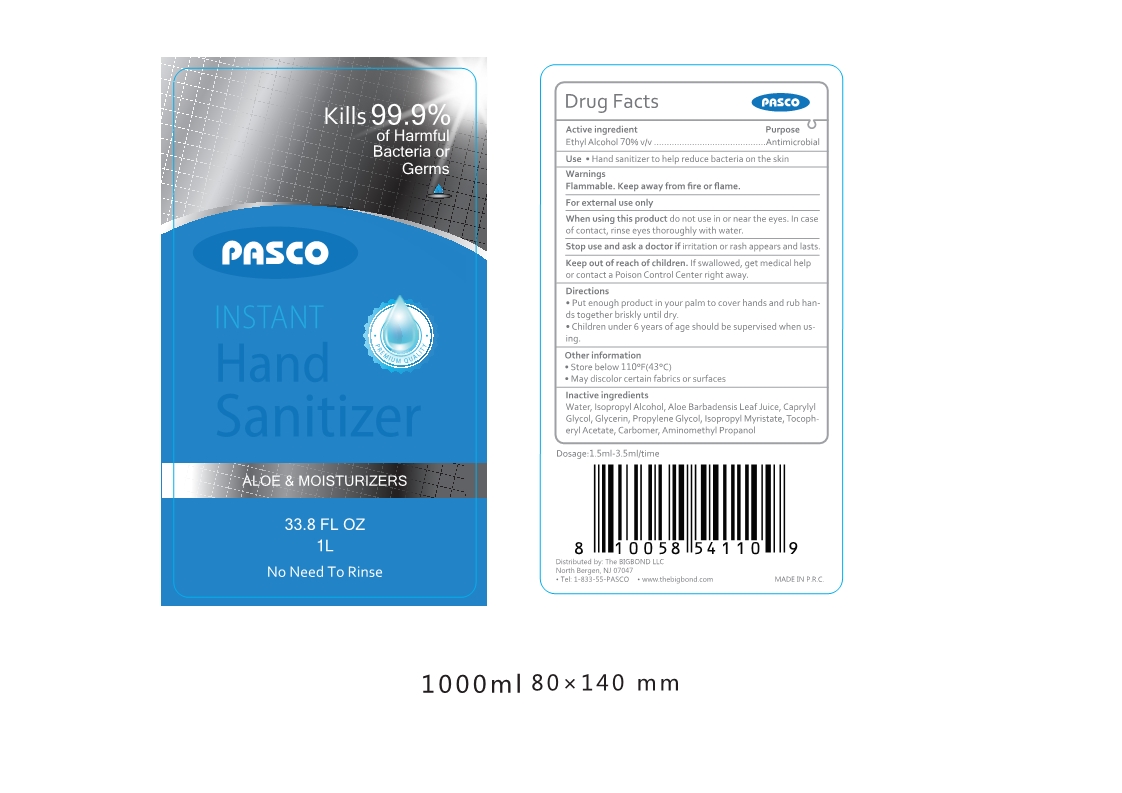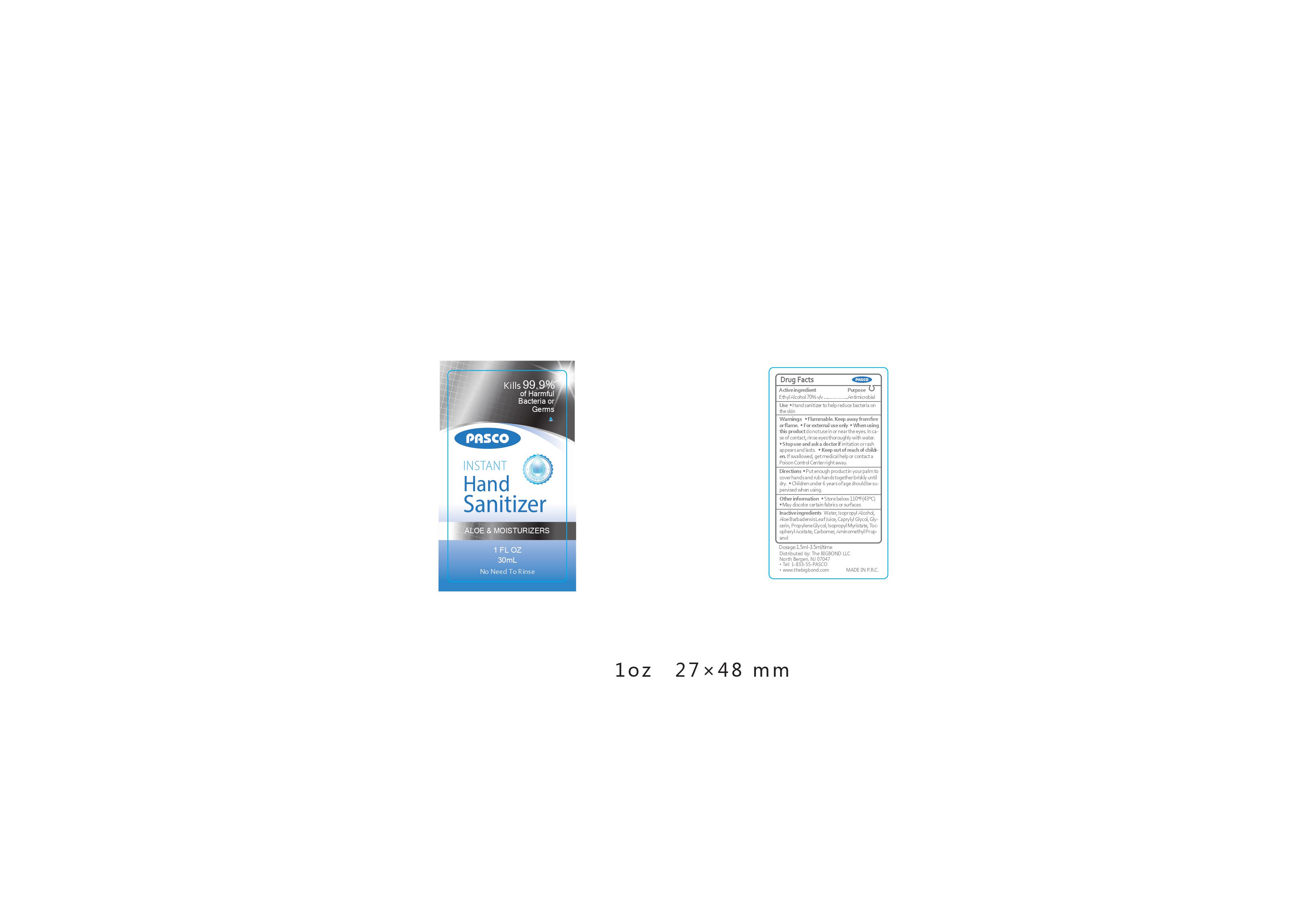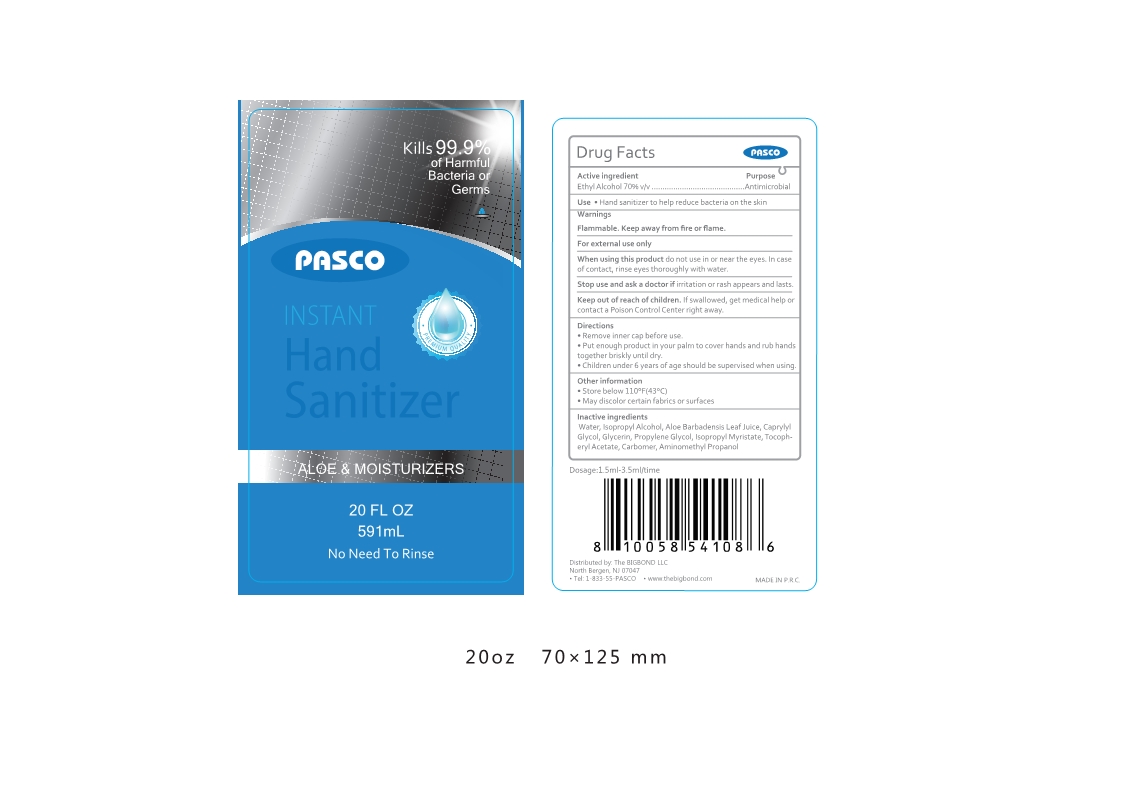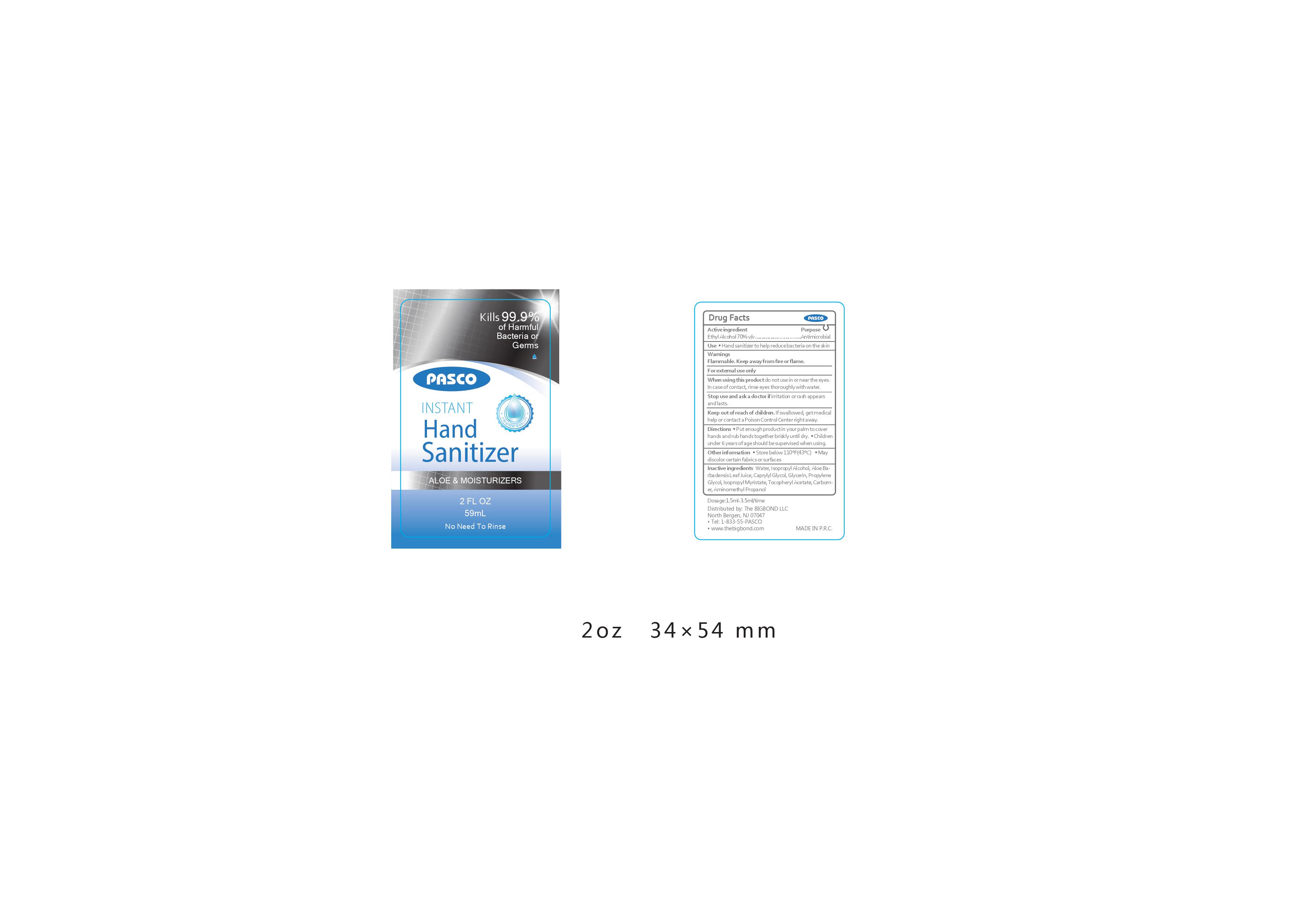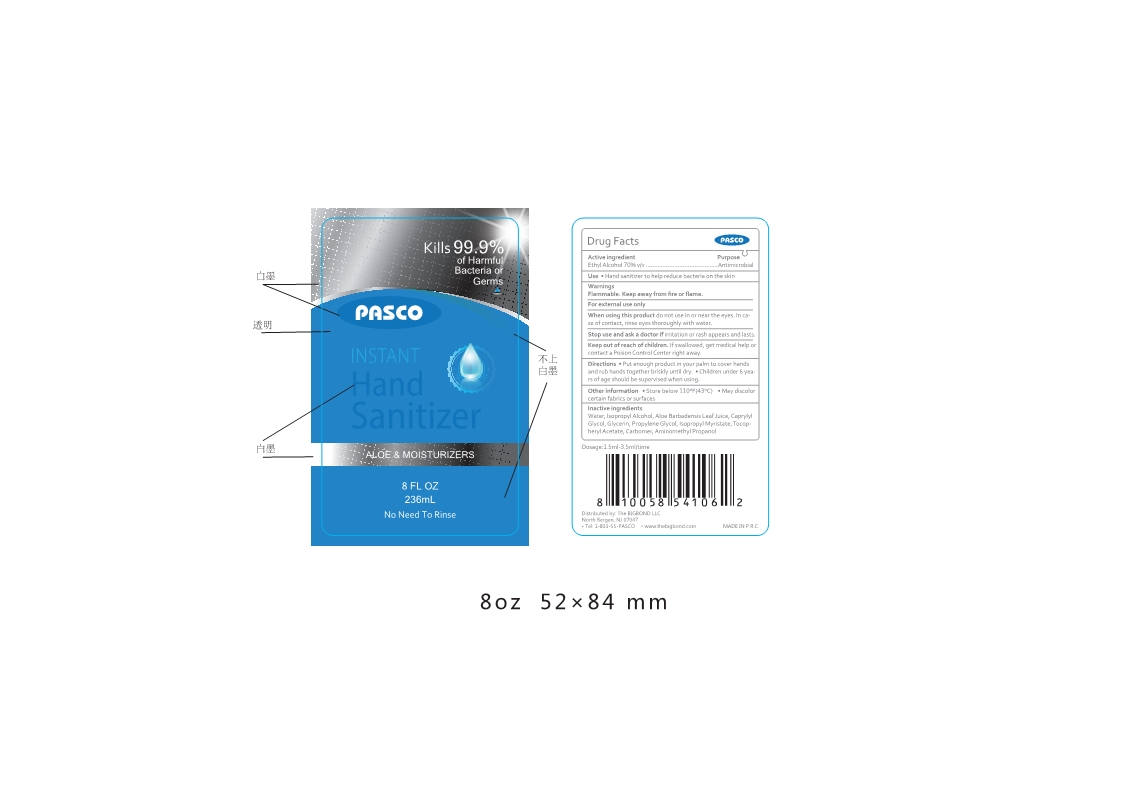 DRUG LABEL: Instant Hand Sanitizer
NDC: 52903-051 | Form: LIQUID
Manufacturer: Ningbo Pasco United Industry Co., Ltd
Category: otc | Type: HUMAN OTC DRUG LABEL
Date: 20200804

ACTIVE INGREDIENTS: ALCOHOL 0.7 1/1 1
INACTIVE INGREDIENTS: ISOPROPYL ALCOHOL; ISOPROPYL MYRISTATE; ALOE VERA LEAF; POLYACRYLIC ACID (300000 MW); WATER; CAPRYLYL GLYCOL; PROPYLENE GLYCOL; GLYCERIN; .ALPHA.-TOCOPHEROL ACETATE; AMINOMETHYLPROPANOL

WUYUN Hand Sanitizer

Active Ingredient(s)

Alcohol 70% v/v. Purpose: Antimicrobial

Purpose

Antiseptic, Hand Sanitizer

Use

Hand Sanizier to help reduce bacteria on the skin.

Warnings

For external use only. Flammable. Keep away from heat or flame

When using this product do not use in or near the eyes. Incase of contact, rinse eyes thoroughly with water.

Stop use and ask a doctor if irritation or rash appears and lasts.

Keep out of reach of children. If swallowed, get medical help or contact a Poison Control Center right away.

Directions

- Put enough product in your palm to cover hands and rub hands together briskly until dry.
- Children under 6 years of age should be supervised when using.

Other information

- Store below 110℉(43℃)
- May discolor certain fabrics or surfaces.

Inactive ingredients

Water, Isopropyl Alcohol, Aloe Barbadensis Leaf Juice, Caprylyl Glycol, Glycerin, Propylene Glycol, Isopropy Myristate, Tocopheryl Acetate, Carbomer, Aminomethyl Propanol

Package Label - Principal Display Panel

1oz Instant Hand Sanitizer

2floz Instant Hand Sanitizer 88floz Instant Hand Sanitizer

20floz Instant Hand Sanitizer 1L Instant Hand Sanitizer